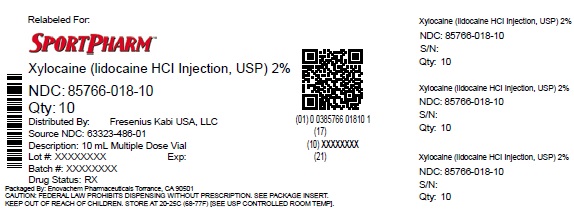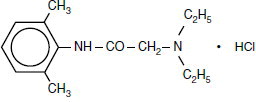 DRUG LABEL: Xylocaine

NDC: 85766-018 | Form: INJECTION, SOLUTION
Manufacturer: Sportpharm LLC
Category: prescription | Type: HUMAN PRESCRIPTION DRUG LABEL
Date: 20260203

ACTIVE INGREDIENTS: LIDOCAINE HYDROCHLORIDE ANHYDROUS 20 mg/1 mL
INACTIVE INGREDIENTS: SODIUM CHLORIDE 6 mg/1 mL; METHYLPARABEN 1 mg/1 mL; SODIUM HYDROXIDE; HYDROCHLORIC ACID

Xylocaine®
(lidocaine HCl Injection, USP)

For Infiltration and Nerve Block

Rx only

DESCRIPTION

Xylocaine (lidocaine HCl) Injections are sterile, nonpyrogenic, aqueous solutions that contain a local anesthetic agent and are administered parenterally by injection. See INDICATIONS AND USAGEsection for specific uses.

Xylocaine solutions contain lidocaine HCl, which is chemically designated as acetamide, 2-(diethylamino)-N-(2,6-dimethylphenyl)-, monohydrochloride and has the molecular wt. 270.8. Lidocaine HCl (C14H22N2O • HCl) has the following structural formula:

CLINICAL PHARMACOLOGY

Mechanism of Action

Lidocaine HCl stabilizes the neuronal membrane by inhibiting the ionic fluxes required for the initiation and conduction of impulses thereby effecting local anesthetic action.

Hemodynamics

Excessive blood levels may cause changes in cardiac output, total peripheral resistance, and mean arterial pressure. With central neural blockade these changes may be attributable to block of autonomic fibers, a direct depressant effect of the local anesthetic agent on various components of the cardiovascular system, and/or the beta-adrenergic receptor stimulating action of epinephrine when present. The net effect is normally a modest hypotension when the recommended dosages are not exceeded.

Pharmacokinetics and Metabolism

Information derived from diverse formulations, concentrations and usages reveals that lidocaine HCl is completely absorbed following parenteral administration, its rate of absorption depending, for example, upon various factors such as the site of administration and the presence or absence of a vasoconstrictor agent. Except for intravascular administration, the highest blood levels are obtained following intercostal nerve block and the lowest after subcutaneous administration.

The plasma binding of lidocaine HCl is dependent on drug concentration, and the fraction bound decreases with increasing concentration. At concentrations of 1 to 4 mcg of free base per mL 60 to 80 percent of lidocaine HCl is protein bound. Binding is also dependent on the plasma concentration of the alpha-1-acid glycoprotein.

Lidocaine HCl crosses the blood-brain and placental barriers, presumably by passive diffusion.

Lidocaine HCl is metabolized rapidly by the liver, and metabolites and unchanged drug are excreted by the kidneys. Biotransformation includes oxidative N-dealkylation, ring hydroxylation, cleavage of the amide linkage, and conjugation. N-dealkylation, a major pathway of biotransformation, yields the metabolites monoethylglycinexylidide and glycinexylidide. The pharmacological/toxicological actions of these metabolites are similar to, but less potent than, those of lidocaine HCl. Approximately 90% of lidocaine HCl administered is excreted in the form of various metabolites, and less than 10% is excreted unchanged. The primary metabolite in urine is a conjugate of 4-hydroxy-2,6-dimethylaniline.

The elimination half-life of lidocaine HCl following an intravenous bolus injection is typically 1.5 to 2 hours. Because of the rapid rate at which lidocaine HCl is metabolized, any condition that affects liver function may alter lidocaine HCl kinetics. The half-life may be prolonged two-fold or more in patients with liver dysfunction. Renal dysfunction does not affect lidocaine HCl kinetics but may increase the accumulation of metabolites.

Factors such as acidosis and the use of CNS stimulants and depressants affect the CNS levels of lidocaine HCl required to produce overt systemic effects. Objective adverse manifestations become increasingly apparent with increasing venous plasma levels above 6 mcg free base per mL. In the rhesus monkey arterial blood levels of 18 to 21 mcg/mL have been shown to be threshold for convulsive activity.

INDICATIONS AND USAGE

Xylocaine (lidocaine HCl) Injections are indicated for production of local or regional anesthesia by infiltration techniques such as percutaneous injection and intravenous regional anesthesia by peripheral nerve block techniques such as brachial plexus and intercostal and by central neural techniques such as lumbar and caudal epidural blocks, when the accepted procedures for these techniques as described in standard textbooks are observed.

CONTRAINDICATIONS

Lidocaine HCl is contraindicated in patients with a known history of hypersensitivity to local anesthetics of the amide type.

WARNINGS

XYLOCAINE INJECTIONS FOR INFILTRATION AND NERVE BLOCK SHOULD BE EMPLOYED ONLY BY CLINICIANS WHO ARE WELL VERSED IN DIAGNOSIS AND MANAGEMENT OF DOSE-RELATED TOXICITY AND OTHER ACUTE EMERGENCIES THAT MIGHT ARISE FROM THE BLOCK TO BE EMPLOYED AND THEN ONLY AFTER ENSURING THE IMMEDIATEAVAILABILITY OF OXYGEN, OTHER RESUSCITATIVE DRUGS, CARDIOPULMONARY EQUIPMENT AND THE PERSONNEL NEEDED FOR PROPER MANAGEMENT OF TOXIC REACTIONS AND RELATED EMERGENCIES (see also ADVERSE REACTIONSand PRECAUTIONS). DELAY IN PROPER MANAGEMENT OF DOSE-RELATED TOXICITY, UNDERVENTILATION FROM ANY CAUSE AND/OR ALTERED SENSITIVITY MAY LEAD TO THE DEVELOPMENT OF ACIDOSIS, CARDIAC ARREST AND, POSSIBLY, DEATH.

Methemoglobinemia

Cases of methemoglobinemia have been reported in association with local anesthetic use. Although all patients are at risk for methemoglobinemia, patients with glucose-6-phosphate dehydrogenase deficiency, congenital or idiopathic methemoglobinemia, cardiac or pulmonary compromise, infants under 6 months of age, and concurrent exposure to oxidizing agents or their metabolites are more susceptible to developing clinical manifestations of the condition. If local anesthetics must be used in these patients, close monitoring for symptoms and signs of methemoglobinemia is recommended.

Signs of methemoglobinemia may occur immediately or may be delayed some hours after exposure, and are characterized by a cyanotic skin discoloration and/or abnormal coloration of the blood. Methemoglobin levels may continue to rise; therefore, immediate treatment is required to avert more serious central nervous system and cardiovascular adverse effects, including seizures, coma, arrhythmias, and death. Discontinue Xylocaine and any other oxidizing agents. Depending on the severity of the signs and symptoms, patients may respond to supportive care, i.e., oxygen therapy, hydration. A more severe clinical presentation may require treatment with methylene blue, exchange transfusion, or hyperbaric oxygen.

Intra-articular infusions of local anesthetics following arthroscopic and other surgical procedures is an unapproved use, and there have been post-marketing reports of chondrolysis in patients receiving such infusions. The majority of reported cases of chondrolysis have involved the shoulder joint; cases of gleno-humeral chondrolysis have been described in pediatric and adult patients following intra-articular infusions of local anesthetics with and without epinephrine for periods of 48 to 72 hours. There is insufficient information to determine whether shorter infusion periods are not associated with these findings. The time of onset of symptoms, such as joint pain, stiffness and loss of motion can be variable, but may begin as early as the 2nd month after surgery. Currently, there is no effective treatment for chondrolysis; patients who experienced chondrolysis have required additional diagnostic and therapeutic procedures and some required arthroplasty or shoulder replacement.

To avoid intravascular injection, aspiration should be performed before the local anesthetic solution is injected. The needle must be repositioned until no return of blood can be elicited by aspiration. Note, however, that the absence of blood in the syringe does not guarantee that intravascular injection has been avoided.

Local anesthetic solutions containing antimicrobial preservatives (e.g., methylparaben) should not be used for epidural or spinal anesthesia because the safety of these agents has not been established with regard to intrathecal injection, either intentional or accidental.

Xylocaine with epinephrine solutions contain sodium metabisulfite, a sulfite that may cause allergic-type reactions including anaphylactic symptoms and life-threatening or less severe asthmatic episodes in certain susceptible people. The overall prevalence of sulfite sensitivity in the general population is unknown and probably low. Sulfite sensitivity is seen more frequently in asthmatic than in non-asthmatic people.
Anaphylactic reactions may occur following administration of lidocaine hydrochloride (see ADVERSE REACTIONS).
In the case of severe reaction, discontinue the use of the drug.

PRECAUTIONS

General

The safety and effectiveness of lidocaine HCl depend on proper dosage, correct technique, adequate precautions, and readiness for emergencies. Standard textbooks should be consulted for specific techniques and precautions for various regional anesthetic procedures.

Resuscitative equipment, oxygen, and other resuscitative drugs should be available for immediate use (see WARNINGSand ADVERSE REACTIONS). The lowest dosage that results in effective anesthesia should be used to avoid high plasma levels and serious adverse effects. Syringe aspirations should also be performed before and during each supplemental injection when using indwelling catheter techniques. During the administration of epidural anesthesia, it is recommended that a test dose be administered initially and that the patient be monitored for central nervous system toxicity and cardiovascular toxicity, as well as for signs of unintended intrathecal administration, before proceeding. When clinical conditions permit, consideration should be given to employing local anesthetic solutions that contain epinephrine for the test dose because circulatory changes compatible with epinephrine may also serve as a warning sign of unintended intravascular injection. An intravascular injection is still possible even if aspirations for blood are negative. Repeated doses of lidocaine HCl may cause significant increases in blood levels with each repeated dose because of slow accumulation of the drug or its metabolites. Tolerance to elevated blood levels varies with the status of the patient. Debilitated, elderly patients, acutely ill patients, and children should be given reduced doses commensurate with their age and physical condition. Lidocaine HCl should also be used with caution in patients with severe shock or heart block.

Lumbar and caudal epidural anesthesia should be used with extreme caution in persons with the following conditions: existing neurological disease, spinal deformities, septicemia, and severe hypertension.

Local anesthetic solutions containing a vasoconstrictor should be used cautiously and in carefully circumscribed quantities in areas of the body supplied by end arteries or having otherwise compromised blood supply. Patients with peripheral vascular disease and those with hypertensive vascular disease may exhibit exaggerated vasoconstrictor response. Ischemic injury or necrosis may result. Preparations containing a vasoconstrictor should be used with caution in patients during or following the administration of potent general anesthetic agents, since cardiac arrhythmias may occur under such conditions.

Careful and constant monitoring of cardiovascular and respiratory (adequacy of ventilation) vital signs and the patient’s state of consciousness should be accomplished after each local anesthetic injection. It should be kept in mind at such times that restlessness, anxiety, tinnitus, dizziness, blurred vision, tremors, depression or drowsiness may be early warning signs of central nervous system toxicity.

Since amide-type local anesthetics are metabolized by the liver, Xylocaine Injection should be used with caution in patients with hepatic disease. Patients with severe hepatic disease, because of their inability to metabolize local anesthetics normally, are at greater risk of developing toxic plasma concentrations. Xylocaine Injection should also be used with caution in patients with impaired cardiovascular function since they may be less able to compensate for functional changes associated with the prolongation of A-V conduction produced by these drugs.

Many drugs used during the conduct of anesthesia are considered potential triggering agents for familial malignant hyperthermia. Since it is not known whether amide-type local anesthetics may trigger this reaction and since the need for supplemental general anesthesia cannot be predicted in advance, it is suggested that a standard protocol for the management of malignant hyperthermia should be available. Early unexplained signs of tachycardia, tachypnea, labile blood pressure and metabolic acidosis may precede temperature elevation. Successful outcome is dependent on early diagnosis, prompt discontinuance of the suspect triggering agent(s) and institution of treatment, including oxygen therapy, indicated supportive measures and dantrolene (consult dantrolene sodium intravenous package insert before using).

Proper tourniquet technique, as described in publications and standard textbooks, is essential in the performance of intravenous regional anesthesia. Solutions containing epinephrine or other vasoconstrictors should not be used for this technique.

Lidocaine HCl should be used with caution in persons with known drug sensitivities. Patients allergic to para-aminobenzoic acid derivatives (procaine, tetracaine, benzocaine, etc.) have not shown cross-sensitivity to lidocaine HCl.

Use in the Head and Neck Area

Small doses of local anesthetics injected into the head and neck area, including retrobulbar, dental and stellate ganglion blocks, may produce adverse reactions similar to systemic toxicity seen with unintentional intravascular injections of larger doses. Confusion, convulsions, respiratory depression and/or respiratory arrest, and cardiovascular stimulation or depression have been reported. These reactions may be due to intra-arterial injection of the local anesthetic with retrograde flow to the cerebral circulation. Patients receiving these blocks should have their circulation and respiration monitored and be constantly observed. Resuscitative equipment and personnel for treating adverse reactions should be immediately available. Dosage recommendations should not be exceeded (see DOSAGE AND ADMINISTRATION).

Information for Patients

When appropriate, patients should be informed in advance that they may experience temporary loss of sensation and motor activity, usually in the lower half of the body, following proper administration of epidural anesthesia.

Inform patients that use of local anesthetics may cause methemoglobinemia, a serious condition that must be treated promptly. Advise patients or caregivers to seek immediate medical attention if they or someone in their care experience the following signs or symptoms: pale, gray, or blue colored skin (cyanosis); headache; rapid heart rate; shortness of breath; lightheadedness; or fatigue.

Clinically Significant Drug Interactions

The administration of local anesthetic solutions containing epinephrine or norepinephrine to patients receiving monoamine oxidase inhibitors or tricyclic antidepressants may produce severe, prolonged hypertension.

Phenothiazines and butyrophenones may reduce or reverse the pressor effect of epinephrine.

Concurrent use of these agents should generally be avoided. In situations when concurrent therapy is necessary, careful patient monitoring is essential.

Concurrent administration of vasopressor drugs (for the treatment of hypotension related to obstetric blocks) and ergot-type oxytocic drugs may cause severe, persistent hypertension or cerebrovascular accidents.

Drug/Laboratory Test Interactions

The intramuscular injection of lidocaine HCl may result in an increase in creatine phosphokinase levels. Thus, the use of this enzyme determination, without isoenzyme separation, as a diagnostic test for the presence of acute myocardial infarction may be compromised by the intramuscular injection of lidocaine HCl.

Patients who are administered local anesthetics are at increased risk of developing methemoglobinemia when concurrently exposed to the following drugs, which could include other local anesthetics:

Examples of Drugs Associated with Methemoglobinemia:

Class | Examples
 | Examples
Nitrates/Nitrites | nitric oxide, nitroglycerin, nitroprusside, nitrous oxide
 | nitric oxide, nitroglycerin, nitroprusside, nitrous oxide
Local anesthetics | articaine, benzocaine, bupivacaine, lidocaine, mepivacaine, prilocaine, procaine, ropivacaine, tetracaine
Antineoplastic agents | cyclophosphamide, flutamide, hydroxyurea, ifosfamide, rasburicase
Antibiotics | dapsone, nitrofurantoin, paraaminosalicylic acid, sulfonamides
Antimalarials | chloroquine, primaquine
Anticonvulsants | Phenobarbital, phenytoin, sodium valproate
Other drugs | acetaminophen, metoclopramide, quinine, sulfasalazine

Carcinogenesis, Mutagenesis, Impairment of Fertility

Studies of lidocaine HCl in animals to evaluate the carcinogenic and mutagenic potential or the effect on fertility have not been conducted.

Pregnancy

Teratogenic Effects: Pregnancy Category B.

Reproduction studies have been performed in rats at doses up to 6.6 times the human dose and have revealed no evidence of harm to the fetus caused by lidocaine HCl. There are, however, no adequate and well-controlled studies in pregnant women. Animal reproduction studies are not always predictive of human response. General consideration should be given to this fact before administering lidocaine HCl to women of childbearing potential, especially during early pregnancy when maximum organogenesis takes place.

Labor and Delivery

Local anesthetics rapidly cross the placenta and when used for epidural, paracervical, pudendal or caudal block anesthesia, can cause varying degrees of maternal, fetal and neonatal toxicity (see CLINICAL PHARMACOLOGY, Pharmacokinetics and Metabolism). The potential for toxicity depends upon the procedure performed, the type and amount of drug used, and the technique of drug administration. Adverse reactions in the parturient, fetus and neonate involve alterations of the central nervous system, peripheral vascular tone and cardiac function.

Maternal hypotension has resulted from regional anesthesia. Local anesthetics produce vasodilation by blocking sympathetic nerves. Elevating the patient’s legs and positioning her on her left side will help prevent decreases in blood pressure.

The fetal heart rate also should be monitored continuously, and electronic fetal monitoring is highly advisable.

Epidural, spinal, paracervical, or pudendal anesthesia may alter the forces of parturition through changes in uterine contractility or maternal expulsive efforts. In one study, paracervical block anesthesia was associated with a decrease in the mean duration of first stage labor and facilitation of cervical dilation. However, spinal and epidural anesthesia have also been reported to prolong the second stage of labor by removing the parturient’s reflex urge to bear down or by interfering with motor function. The use of obstetrical anesthesia may increase the need for forceps assistance.

The use of some local anesthetic drug products during labor and delivery may be followed by diminished muscle strength and tone for the first day or two of life. The long-term significance of these observations is unknown. Fetal bradycardia may occur in 20 to 30 percent of patients receiving paracervical nerve block anesthesia with the amide-type local anesthetics and may be associated with fetal acidosis. Fetal heart rate should always be monitored during paracervical anesthesia. The physician should weigh the possible advantages against risks when considering a paracervical block in prematurity, toxemia of pregnancy, and fetal distress. Careful adherence to recommended dosage is of the utmost importance in obstetrical paracervical block. Failure to achieve adequate analgesia with recommended doses should arouse suspicion of intravascular or fetal intracranial injection. Cases compatible with unintended fetal intracranial injection of local anesthetic solution have been reported following intended paracervical or pudendal block or both. Babies so affected present with unexplained neonatal depression at birth, which correlates with high local anesthetic serum levels, and often manifest seizures within six hours. Prompt use of supportive measures combined with forced urinary excretion of the local anesthetic has been used successfully to manage this complication.

Case reports of maternal convulsions and cardiovascular collapse following use of some local anesthetics for paracervical block in early pregnancy (as anesthesia for elective abortion) suggest that systemic absorption under these circumstances may be rapid. The recommended maximum dose of each drug should not be exceeded. Injection should be made slowly and with frequent aspiration. Allow a 5-minute interval between sides.

Nursing Mothers

It is not known whether this drug is excreted in human milk. Because many drugs are excreted in human milk, caution should be exercised when lidocaine HCl is administered to a nursing woman.

Pediatric Use

Dosages in children should be reduced, commensurate with age, body weight and physical condition, see DOSAGE AND ADMINISTRATION.

ADVERSE REACTIONS

To report SUSPECTED ADVERSE REACTIONS, contact Fresenius Kabi USA, LLC at 1-800-551-7176 or FDA at 1-800-FDA-1088 or www.fda.gov/medwatch.

Systemic

Adverse experiences following the administration of lidocaine HCl are similar in nature to those observed with other amide local anesthetic agents. These adverse experiences are, in general, dose-related and may result from high plasma levels caused by excessive dosage, rapid absorption or inadvertent intravascular injection, or may result from a hypersensitivity, idiosyncrasy or diminished tolerance on the part of the patient. Serious adverse experiences are generally systemic in nature. The following types are those most commonly reported:

Central Nervous System

CNS manifestations are excitatory and/or depressant and may be characterized by lightheadedness, nervousness, apprehension, euphoria, confusion, dizziness, drowsiness, tinnitus, blurred or double vision, vomiting, sensations of heat, cold or numbness, twitching, tremors, convulsions, unconsciousness, respiratory depression and arrest. The excitatory manifestations may be very brief or may not occur at all, in which case the first manifestation of toxicity may be drowsiness merging into unconsciousness and respiratory arrest.

Drowsiness following the administration of lidocaine HCl is usually an early sign of a high blood level of the drug and may occur as a consequence of rapid absorption.

Cardiovascular System

Cardiovascular manifestations are usually depressant and are characterized by bradycardia, hypotension, and cardiovascular collapse, which may lead to cardiac arrest.

Allergic

Allergic reactions are characterized by cutaneous lesions, urticaria, edema or anaphylactoid reactions. Allergic reactions may occur as a result of sensitivity either to local anesthetic agents or to the methylparaben used as a preservative in the multiple dose vials. Allergic reactions, including anaphylactic reactions, may occur as a result of sensitivity to lidocaine, but are infrequent. If allergic reactions do occur, they should be managed by conventional means. The detection of sensitivity by skin testing is of doubtful value.
There have been no reports of cross sensitivity between lidocaine hydrochloride and procainamide or between lidocaine hydrochloride and quinidine.

Neurologic

The incidences of adverse reactions associated with the use of local anesthetics may be related to the total dose of local anesthetic administered and are also dependent upon the particular drug used, the route of administration and the physical status of the patient. In a prospective review of 10,440 patients who received lidocaine HCl for spinal anesthesia, the incidences of adverse reactions were reported to be about 3 percent each for positional headaches, hypotension and backache; 2 percent for shivering; and less than 1 percent each for peripheral nerve symptoms, nausea, respiratory inadequacy and double vision. Many of these observations may be related to local anesthetic techniques, with or without a contribution from the local anesthetic.

In the practice of caudal or lumbar epidural block, occasional unintentional penetration of the subarachnoid space by the catheter may occur. Subsequent adverse effects may depend partially on the amount of drug administered subdurally. These may include spinal block of varying magnitude (including total spinal block), hypotension secondary to spinal block, loss of bladder and bowel control, and loss of perineal sensation and sexual function. Persistent motor, sensory and/or autonomic (sphincter control) deficit of some lower spinal segments with slow recovery (several months) or incomplete recovery have been reported in rare instances when caudal or lumbar epidural block has been attempted. Backache and headache have also been noted following use of these anesthetic procedures.

There have been reported cases of permanent injury to extraocular muscles requiring surgical repair following retrobulbar administration.
Hematologic
Methemoglobinemia.

OVERDOSAGE

Acute emergencies from local anesthetics are generally related to high plasma levels encountered during therapeutic use of local anesthetics or to unintended subarachnoid injection of local anesthetic solution (see ADVERSE REACTIONS, WARNINGS,and PRECAUTIONS).

Management of Local Anesthetic Emergencies

The first consideration is prevention, best accomplished by careful and constant monitoring of cardiovascular and respiratory vital signs and the patient’s state of consciousness after each local anesthetic injection. At the first sign of change, oxygen should be administered.

The first step in the management of convulsions, as well as underventilation or apnea due to unintended subarachnoid injection of drug solution, consists of immediate attention to the maintenance of a patent airway and assisted or controlled ventilation with oxygen and a delivery system capable of permitting immediate positive airway pressure by mask. Immediately after the institution of these ventilatory measures, the adequacy of the circulation should be evaluated, keeping in mind that drugs used to treat convulsions sometimes depress the circulation when administered intravenously. Should convulsions persist despite adequate respiratory support, and if the status of the circulation permits, small increments of an ultra-short acting barbiturate (such as thiopental or thiamylal) or a benzodiazepine (such as diazepam) may be administered intravenously. The clinician should be familiar, prior to the use of local anesthetics, with these anticonvulsant drugs. Supportive treatment of circulatory depression may require administration of intravenous fluids and, when appropriate, a vasopressor as directed by the clinical situation (e.g., ephedrine).

If not treated immediately, both convulsions and cardiovascular depression can result in hypoxia, acidosis, bradycardia, arrhythmias and cardiac arrest. Underventilation or apnea due to unintentional subarachnoid injection of local anesthetic solution may produce these same signs and also lead to cardiac arrest if ventilatory support is not instituted. If cardiac arrest should occur, standard cardiopulmonary resuscitative measures should be instituted.

Endotracheal intubation, employing drugs and techniques familiar to the clinician, may be indicated, after initial administration of oxygen by mask, if difficulty is encountered in the maintenance of a patent airway or if prolonged ventilatory support (assisted or controlled) is indicated.

Dialysis is of negligible value in the treatment of acute overdosage with lidocaine HCl.

The oral LD50of lidocaine HCl in non-fasted female rats is 459 (346 to 773) mg/kg (as the salt) and 214 (159 to 324) mg/kg (as the salt) in fasted female rats.

DOSAGE AND ADMINISTRATION

Table 1 (Recommended Dosages) summarizes the recommended volumes and concentrations of Xylocaine Injection for various types of anesthetic procedures. The dosages suggested in this table are for normal healthy adults and refer to the use of epinephrine-free solutions. When larger volumes are required, only solutions containing epinephrine should be used except in those cases where vasopressor drugs may be contraindicated.

There have been adverse event reports of chondrolysis in patients receiving intra-articular infusions of local anesthetics following arthroscopic and other surgical procedures. Xylocaine is not approved for this use (see WARNINGSand DOSAGE AND ADMINISTRATION).

These recommended doses serve only as a guide to the amount of anesthetic required for most routine procedures. The actual volumes and concentrations to be used depend on a number of factors such as type and extent of surgical procedure, depth of anesthesia and degree of muscular relaxation required, duration of anesthesia required, and the physical condition of the patient. In all cases the lowest concentration and smallest dose that will produce the desired result should be given. Dosages should be reduced for children and for the elderly and debilitated patients and patients with cardiac and/or liver disease.

The onset of anesthesia, the duration of anesthesia and the degree of muscular relaxation are proportional to the volume and concentration (i.e., total dose) of local anesthetic used. Thus, an increase in volume and concentration of Xylocaine Injection will decrease the onset of anesthesia, prolong the duration of anesthesia, provide a greater degree of muscular relaxation and increase the segmental spread of anesthesia. However, increasing the volume and concentration of Xylocaine Injection may result in a more profound fall in blood pressure when used in epidural anesthesia. Although the incidence of side effects with lidocaine HCl is quite low, caution should be exercised when employing large volumes and concentrations, since the incidence of side effects is directly proportional to the total dose of local anesthetic agent injected.

For intravenous regional anesthesia, only the 50 mL single dose vial containing Xylocaine (lidocaine HCl) 0.5% Injection should be used.

Epidural Anesthesia

For epidural anesthesia, only the following dosage forms of Xylocaine Injection are recommended:

1% without epinephrine 10 mL Plastic Ampule

1% without epinephrine 30 mL single dose solutions

1% with epinephrine 1:200,000 30 mL single dose solutions

1.5% without epinephrine 10 mL Plastic Ampule

1.5% without epinephrine 20 mL Plastic Ampule

1.5% with epinephrine 1:200,000 30 mL ampules, 30 mL single dose solutions

2% without epinephrine 10 mL Plastic Ampule

2% with epinephrine 1:200,000 20 mL ampules, 20 mL single dose solutions

Although these solutions are intended specifically for epidural anesthesia, they may also be used for infiltration and peripheral nerve block, provided they are employed as single dose units. These solutions contain no bacteriostatic agent.

In epidural anesthesia, the dosage varies with the number of dermatomes to be anesthetized (generally 2 to 3 mL of the indicated concentration per dermatome).

Caudal and Lumbar Epidural Block

As a precaution against the adverse experience sometimes observed following unintentional penetration of the subarachnoid space, a test dose such as 2 to 3 mL of 1.5% lidocaine HCl should be administered at least 5 minutes prior to injecting the total volume required for a lumbar or caudal epidural block. The test dose should be repeated if the patient is moved in a manner that may have displaced the catheter. Epinephrine, if contained in the test dose (10 to 15 mcg have been suggested), may serve as a warning of unintentional intravascular injection. If injected into a blood vessel, this amount of epinephrine is likely to produce a transient “epinephrine response” within 45 seconds, consisting of an increase in heart rate and systolic blood pressure, circumoral pallor, palpitations and nervousness in the unsedated patient. The sedated patient may exhibit only a pulse rate increase of 20 or more beats per minute for 15 or more seconds. Patients on beta blockers may not manifest changes in heart rate, but blood pressure monitoring can detect an evanescent rise in systolic blood pressure. Adequate time should be allowed for onset of anesthesia after administration of each test dose. The rapid injection of a large volume of Xylocaine Injection through the catheter should be avoided, and, when feasible, fractional doses should be administered.

In the event of the known injection of a large volume of local anesthetic solution into the subarachnoid space, after suitable resuscitation and if the catheter is in place, consider attempting the recovery of drug by draining a moderate amount of cerebrospinal fluid (such as 10 mL) through the epidural catheter.

MAXIMUM RECOMMENDED DOSAGES

Adults

For normal healthy adults, the individual maximum recommended dose of lidocaine HCl with epinephrine should not exceed 7 mg/kg (3.5 mg/lb) of body weight, and in general it is recommended that the maximum total dose not exceed 500 mg. When used without epinephrine the maximum individual dose should not exceed 4.5 mg/kg (2 mg/lb) of body weight, and in general it is recommended that the maximum total dose does not exceed 300 mg. For continuous epidural or caudal anesthesia, the maximum recommended dosage should not be administered at intervals of less than 90 minutes. When continuous lumbar or caudal epidural anesthesia is used for non-obstetrical procedures, more drug may be administered if required to produce adequate anesthesia.

The maximum recommended dose per 90 minute period of lidocaine hydrochloride for paracervical block in obstetrical patients and non-obstetrical patients is 200 mg total. One half of the total dose is usually administered to each side. Inject slowly, five minutes between sides (see also discussion of paracervical block in PRECAUTIONS).

For intravenous regional anesthesia, the dose administered should not exceed 4 mg/kg in adults.

Children

It is difficult to recommend a maximum dose of any drug for children, since this varies as a function of age and weight. For children over 3 years of age who have a normal lean body mass and normal body development, the maximum dose is determined by the child’s age and weight. For example, in a child of 5 years weighing 50 lbs the dose of lidocaine HCl should not exceed 75 to 100 mg (1.5 to 2 mg/lb). The use of even more dilute solutions (i.e., 0.25 to 0.5%) and total dosages not to exceed 3 mg/kg (1.4 mg/lb) are recommended for induction of intravenous regional anesthesia in children.

In order to guard against systemic toxicity, the lowest effective concentration and lowest effective dose should be used at all times. In some cases it will be necessary to dilute available concentrations with 0.9% sodium chloride injection in order to obtain the required final concentration.

NOTE: Parenteral drug products should be inspected visually for particulate matter and discoloration prior to administration whenever the solution and container permit. The Injection is not to be used if its color is pinkish or darker than slightly yellow or if it contains a precipitate.

Table 1: Recommended Dosages

Procedure | Xylocaine (lidocaine hydrochloride) Injection (without epinephrine)
Procedure | Conc (%) | Vol (mL) | Total Dose (mg)
Infiltration
Percutaneous | 0.5 or 1 | 1 to 60 | 5 to 300
Intravenous regional | 0.5 | 10 to 60 | 50 to 300
Peripheral Nerve Blocks, e.g.,
Brachial | 1.5 | 15 to 20 | 225 to 300
Dental | 2 | 1 to 5 | 20 to 100
Intercostal | 1 | 3 | 30
Paravertebral | 1 | 3 to 5 | 30 to 50
Pudendal (each side) | 1 | 10 | 100
Paracervical
Obstetrical analgesia
(each side) | 1 | 10 | 100
Sympathetic Nerve Blocks, e.g.,
Cervical (stellate ganglion) | 1 | 5 | 50
Lumbar | 1 | 5 to 10 | 50 to 100
Central Neural Blocks
Epidural*
Thoracic | 1 | 20 to 30 | 200 to 300
Lumbar
Analgesia | 1 | 25 to 30 | 250 to 300
Anesthesia | 1.5 | 15 to 20 | 225 to 300
 | 2 | 10 to 15 | 200 to 300
Caudal
Obstetrical analgesia | 1 | 20 to 30 | 200 to 300
Surgical anesthesia | 1.5 | 15 to 20 | 225 to 300

*Dose determined by number of dermatomes to be anesthetized (2 to 3 mL/dermatome).

THE ABOVE SUGGESTED CONCENTRATIONS AND VOLUMES SERVE ONLY AS A GUIDE. OTHER VOLUMES AND CONCENTRATIONS MAY BE USED PROVIDED THE TOTAL MAXIMUM RECOMMENDED DOSE IS NOT EXCEEDED.

STERILIZATION, STORAGE AND TECHNICAL PROCEDURES

Disinfecting agents containing heavy metals, which cause release of respective ions (mercury, zinc, copper, etc) should not be used for skin or mucous membrane disinfection as they have been related to incidents of swelling and edema. When chemical disinfection of multi-dose vials is desired, either isopropyl alcohol (91%) or ethyl alcohol (70%) is recommended. Many commercially available brands of rubbing alcohol, as well as solutions of ethyl alcohol not of USP grade, contain denaturants which are injurious to rubber and therefore are not to be used.

Dosage forms listed as Xylocaine-MPF indicate single dose solutions that are Methyl Paraben Free (MPF).

HOW SUPPLIED:

Xylocaine®(lidocaine HCl Injection, USP) 2% 200 mg per 10 mL (20 mg per mL)

10 mL Multiple Dose Vial NDC 85766-018-10 (relabeled from NDC NDC 63323-486-01)

For single-dose vials and ampules: Discard unused portion.

All solutions should be stored at 20° to 25°C (68° to 77°F) [see USP Controlled Room Temperature].

Protect from light.

All trademarks are the property of Fresenius Kabi USA, LLC.

Distributed by:

Sportpharm LLC

379 Van Ness Ave 1401,

Torrance, CA 90501

Relabeled by:

Enovachem PHARMACEUTICALS

Torrance, CA 90501